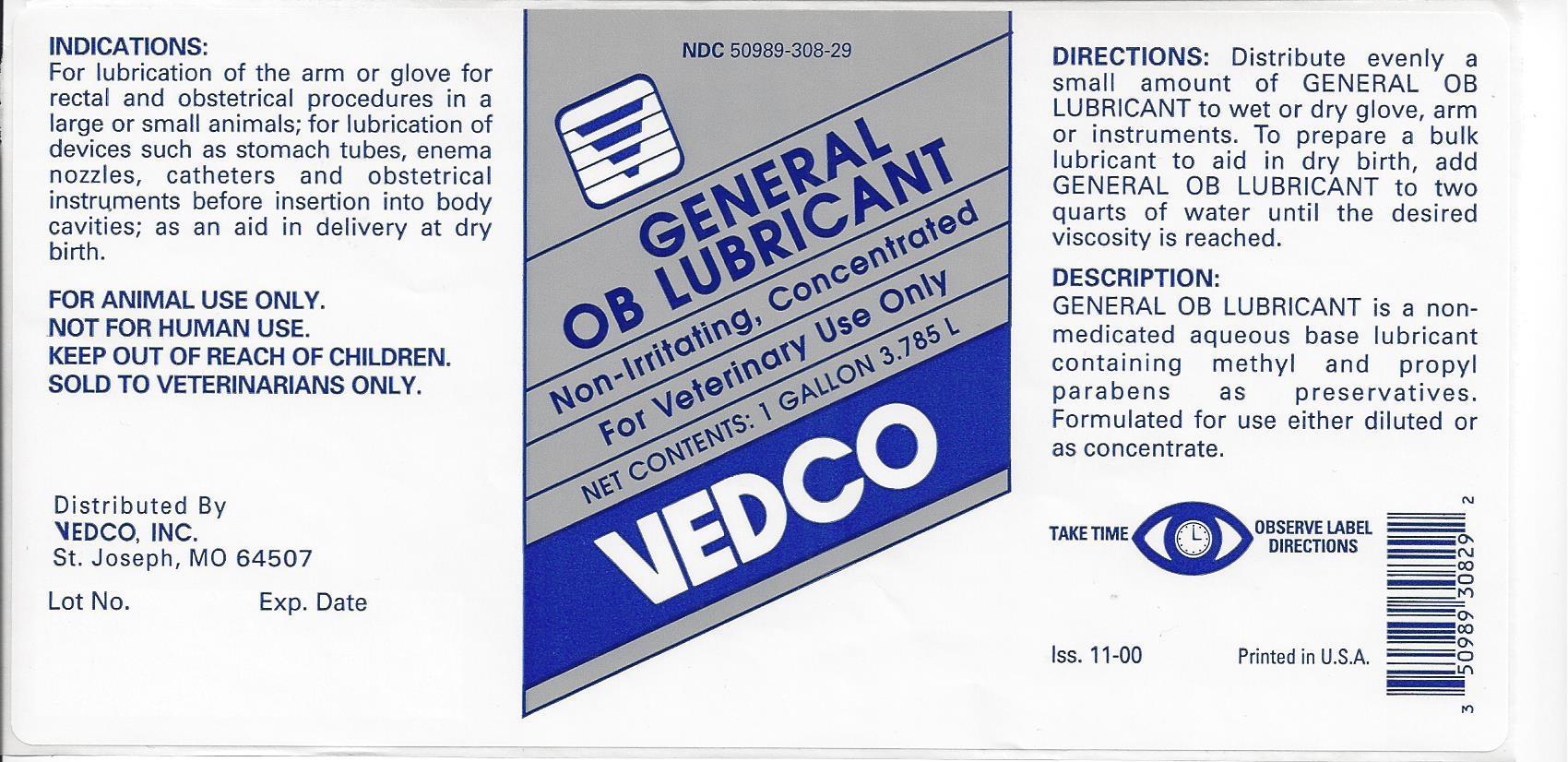 DRUG LABEL: GENERAL OB LUBRICANT
NDC: 50989-308 | Form: LIQUID
Manufacturer: VEDCO
Category: animal | Type: OTC ANIMAL DRUG LABEL
Date: 20130919

ACTIVE INGREDIENTS: PROPYLENE GLYCOL 25.9 mg/1 mL
INACTIVE INGREDIENTS: HYDROXYETHYL CELLULOSE (4000 CPS AT 1%); GLYCERIN; METHYLPARABEN; PROPYLPARABEN; WATER

VEDCO GENERAL OB LUBRICANT

NDC 50989-308-29 GENERAL OB LUBRICANT Non-Irritating, Concentrated For Veterinary Use Only NET CONTENTS: 1 GALLON 3.875L

VEDCO

INDICATION:

For lubricantion of the arm or glove for rectal and obstetrical procedures in a large or small animals; for lubrication of devices such as stomach tubes, enema nozzles, catheters and obstetrical instruments before insertion into body cavities; as an aid in delivery at dry birth.

FOR ANIMAL USE ONLY.

NOT FOR HUMAN USE.

KEEP OUT OF REACH OF CHILDREN.

SOLD TO VETERINARIANS ONLY.

Distributed By

VEDCO, INC.

St. Joseph, MO 64507

Lot No. Exp. Date

DIRECTIONS:

Distribute evenly a small amount of GENERAL OB LUBRICANT to wet or dry glove, arm or instruments. To prepare a bulk lubricant to aid in dry birth, add GENERAL OB LUBRICANT to two quarts of water until the desired viscosity is reached.

DESCRIPTION:

GENERAL OB LUBRICANT is a non-medicated aqueous base lubricant containing methyl and propyl parabens as preseratives. Formulated for use either diluted or as concentrate.

TAKE TIME OBSERVE LABEL DIRECTIONS

Iss. 11-00

Printed in the U.S.A.